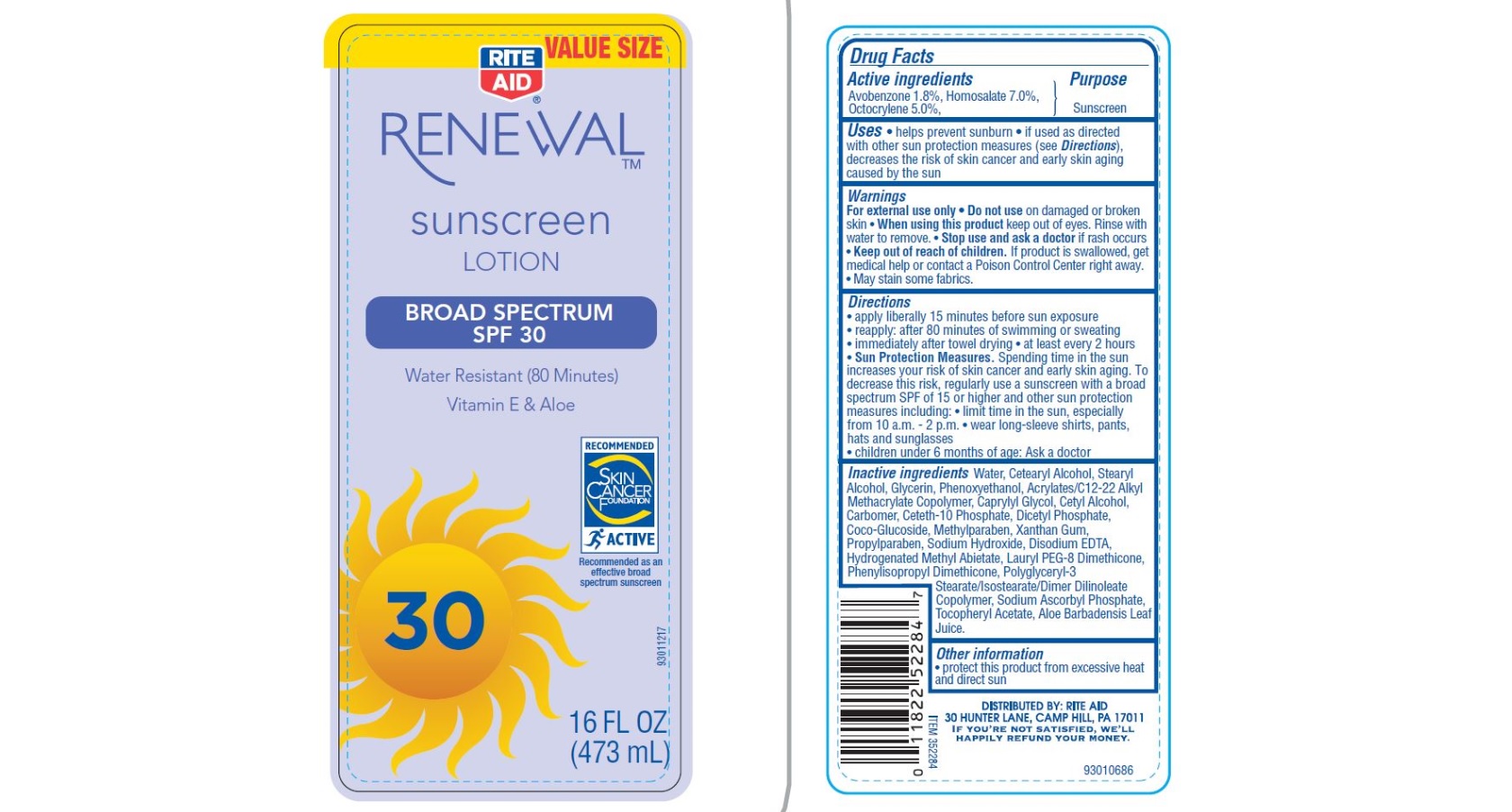 DRUG LABEL: Rite Aid  SPF 30
NDC: 11822-9028 | Form: LOTION
Manufacturer: Rite Aid
Category: otc | Type: HUMAN OTC DRUG LABEL
Date: 20160531

ACTIVE INGREDIENTS: AVOBENZONE 1.8 g/100 g; HOMOSALATE 7 g/100 g; OCTOCRYLENE 5 g/100 g
INACTIVE INGREDIENTS: WATER; CETOSTEARYL ALCOHOL; STEARYL ALCOHOL; GLYCERIN; PHENOXYETHANOL; CAPRYLYL GLYCOL; CETYL ALCOHOL; CARBOXYPOLYMETHYLENE; CETETH-10 PHOSPHATE; DIHEXADECYL PHOSPHATE; COCO GLUCOSIDE; METHYLPARABEN; XANTHAN GUM; PROPYLPARABEN; SODIUM HYDROXIDE; EDETATE DISODIUM; HYDROGENATED METHYL ABIETATE; SODIUM ASCORBYL PHOSPHATE; .ALPHA.-TOCOPHEROL ACETATE; ALOE VERA LEAF

Drug facts

Active ingredients

Avobenzone 1.8%, Homosalate 7.0%, Octocrylene 5.0%

Purpose

Sunscreen

Uses

- helps prevent sunburn
- if used as directed with other sun protection measures (see Directions), decreases the risk of skin cancer and early skin aging caused by the sun

Warnings

For external use only

Do not use

on damaged or broken skin

When using this product

keep out of eyes. Rinse with water to remove

Stop use and ask a doctor

if rash occurs

Keep out of reach of children

If product is swallowed, get medical help or contact a Poison Control Center right away.

- May stain some fabrics.

Directions

- apply liberally 15 minutes before sun exposure
- reapply: after 80 minutes of swimming or sweating
- immediately after towel drying
- at least every 2 hours

- Sun Protection Measures.Spending time in the sun increases your risk of skin cancer and early skin aging. To decrease this risk, regularly use a sunscreen with a broad spectrum SPF of 15 or higher and other sun protection measures including:
- limit time in the sun, especially from 10 a.m. - 2 p.m
- wear long-sleeve shirts, pants, hats and sunglasses
- children under 6 months of age: Ask a doctor

Inactive ingredients

Water, Cetearyl Alcohol, Stearyl Alcohol, Glycerin, Phenoxyethanol, Acrylates/C12-22 Alkyl Methacrylate Copolymer, Caprylyl Glycol, Cetyl Alcohol, Carbomer, Ceteth-10 Phosphate,Dicetyl Phosphate, Coco-Glucoside, Methylparaben, Xanthan Gum, Propylparaben, Sodium Hydroxide, Disodium EDTA, Hydrogenated Methyl Abietate, Lauryl PEG-8 Dimethicone, Phenylisopropyl Dimethicone, Polyglyceryl-3 Stearate/Isostearate/Dimer Dilinoleate Copolymer, Sodium Ascorbyl Phosphate, Tocopheryl Acetate, Aloe Barbadensis Leaf Juice.

Other information

- protect this product from excessive heat and direct sun

Principal Display Panel

11822-9028-9

VALUE SIZE

RITE AID

RENEWAL

sunscreen

LOTION

BROAD SPECTRUM

SPF 30

Water Resistant (80 Minutes)

Vitamin E and Aloe

Recommended

SKIN CANCER FOUNDATION

ACTIVE

Recommended as an effective broad spectrum sunscreen

30

16 FL OZ

(473 mL)